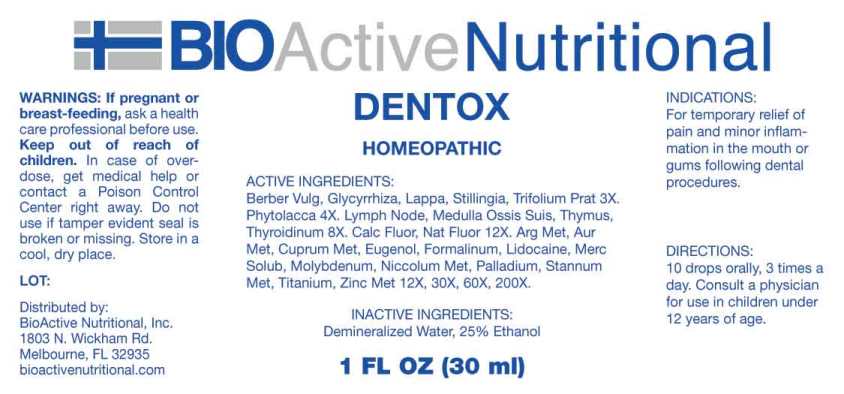 DRUG LABEL: Dentox
NDC: 43857-0593 | Form: LIQUID
Manufacturer: BioActive Nutritional, Inc.
Category: homeopathic | Type: HUMAN OTC DRUG LABEL
Date: 20241017

ACTIVE INGREDIENTS: BERBERIS VULGARIS ROOT BARK 3 [hp_X]/1 mL; GLYCYRRHIZA GLABRA 3 [hp_X]/1 mL; ARCTIUM LAPPA ROOT 3 [hp_X]/1 mL; STILLINGIA SYLVATICA ROOT 3 [hp_X]/1 mL; TRIFOLIUM PRATENSE FLOWER 3 [hp_X]/1 mL; PHYTOLACCA AMERICANA ROOT 4 [hp_X]/1 mL; SUS SCROFA LYMPH 8 [hp_X]/1 mL; SUS SCROFA BONE MARROW 8 [hp_X]/1 mL; SUS SCROFA THYMUS 8 [hp_X]/1 mL; THYROID 8 [hp_X]/1 mL; CALCIUM FLUORIDE 12 [hp_X]/1 mL; SODIUM FLUORIDE 12 [hp_X]/1 mL; SILVER 12 [hp_X]/1 mL; GOLD 12 [hp_X]/1 mL; COPPER 12 [hp_X]/1 mL; EUGENOL 12 [hp_X]/1 mL; FORMALDEHYDE SOLUTION 12 [hp_X]/1 mL; LIDOCAINE 12 [hp_X]/1 mL; MERCURIUS SOLUBILIS 12 [hp_X]/1 mL; MOLYBDENUM 12 [hp_X]/1 mL; NICKEL 12 [hp_X]/1 mL; PALLADIUM 12 [hp_X]/1 mL; TIN 12 [hp_X]/1 mL; TITANIUM 12 [hp_X]/1 mL; ZINC 12 [hp_X]/1 mL
INACTIVE INGREDIENTS: WATER; ALCOHOL

DRUG FACTS:

ACTIVE INGREDIENTS:

Berberis Vulgaris 3X, Glycyrrhiza Glabra 3X, Lappa Major 3X, Stillingia Sylvatica 3X, Trifolium Pratense 3X, Phytolacca Decandra 4X, Lymph (Suis) 8X, Medulla Ossis Suis 8X, Thymus (Suis) 8X,Thyroidinum (Suis) 8X, Calcarea Fluorica 12X, Natrum Fluoratum 12X, Argentum Metallicum 12X, 30X, 60X, 200X, Aurum Metallicum 12X, 30X, 60X, 200X, Cuprum Metallicum 12X, 30X, 60X, 200X, Eugenol 12X, 30X, 60X, 200X, Formalinum 12X, 30X, 60X, 200X, Lidocaine 12X, 30X, 60X, 200X, Mercurius Solubilis 12X, 30X, 60X, 200X, Molybdenum 12X, 30X, 60X, 200X, Niccolum Metallicum 12X, 30X, 60X, 200X, Palladium Metallicum 12X, 30X, 60X, 200X, Stannum Metallicum 12X, 30X, 60X, 200X, Titanium Metallicum 12X, 30X, 60X, 200X, Zincum Metallicum 12X, 30X, 60X, 200X.

PURPOSE:

For temporary relief of pain and minor inflammation in the mouth or gums following dental procedures.

WARNINGS:

If pregnant or breast-feeding, ask a health care professional before use.

Keep out of reach of children. In case of overdose, get medical help or contact a Poison Control Center right away.

Do not use if tamper evident seal is broken or missing.

Store in a cool, dry place.

Keep out of reach of children. In case of overdose, get medical help or contact a Poison Control Center right away.

DIRECTIONS:

10 drops orally, 3 times a day. Consult a physician for use in children under 12 years of age.

INDICATIONS:

For temporary relief of pain and minor inflammation in the mouth or gums following dental procedures.

INACTIVE INGREDIENTS:

Demineralized Water, 25% Ethanol

QUESTIONS:

Distributed by:
BioActive Nutritional, Inc.
1803 N. Wickham Rd.
Melbourne, FL 32935
bioactivenutritional.com

PACKAGE LABEL DISPLAY:

BIOActive Nutritional

DENTOX

HOMEOPATHIC

1 FL OZ (30 ml)